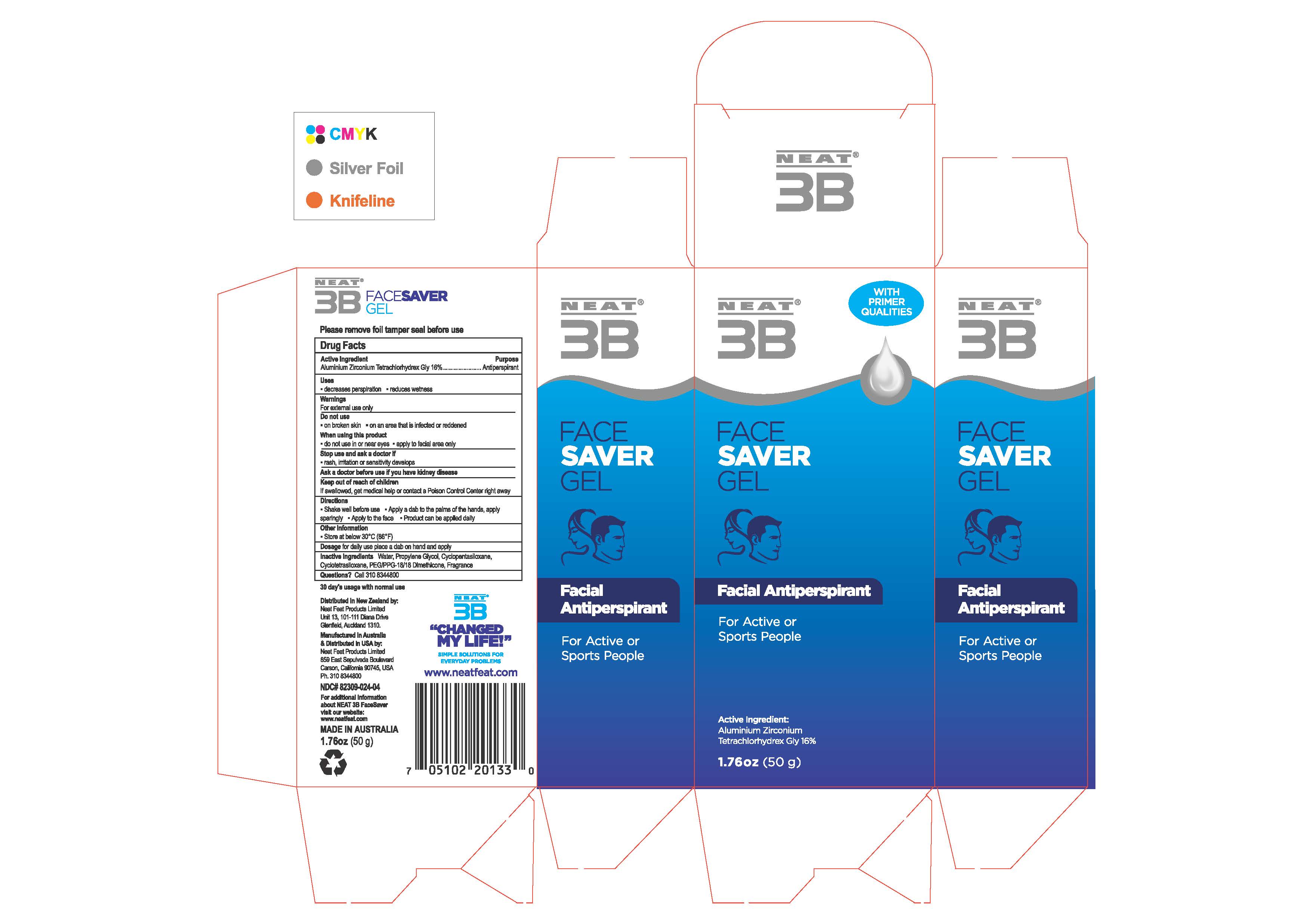 DRUG LABEL: Face Saver Gel
NDC: 82309-024 | Form: GEL
Manufacturer: Tripak Pharmaceuticals
Category: otc | Type: HUMAN OTC DRUG LABEL
Date: 20231101

ACTIVE INGREDIENTS: ALUMINUM ZIRCONIUM TETRACHLOROHYDREX GLY 16 g/100 g
INACTIVE INGREDIENTS: PEG/PPG-18/18 DIMETHICONE; WATER; PROPYLENE GLYCOL; CYCLOMETHICONE 5; CYCLOMETHICONE 4

Face Saver Gel

PACKAGE LABEL

NDC# 82309-024-04

ACTIVE INGREDIENT

Aluminium Zirconium Tetrachlorhydrex Gly 16% Antiperspirant

Uses:

decreases perspiration

reduces wetness

WARNINGS

For external use only

Do not use:

-on broken skin - on an area that is infected or reddened

When using this product
• do not use in or near eyes •apply to facial area only

Stop use and ask a doctor if
• rash, irritation or sensitivity develops
Ask a doctor before use if you have kidney disease

Keep out of reach of children
If swallowed, get medical help or contact a Poison Control Center right away

Directions
• Shake well before use • Apply a dab to the palms of the hands, apply sparingly •Apply to the face •Product can be applied daily

For daily use place a dab on hand and apply

Other information
• Store at below 30 °C(86°F)

INACTIVE INGREDIENT

Inactive ingredients Water, Propylene Glycol, Cydopentasiloxane, Cyclotetrasiloxane, PEG/PPG-18/18 Dimethicone, Fragrance